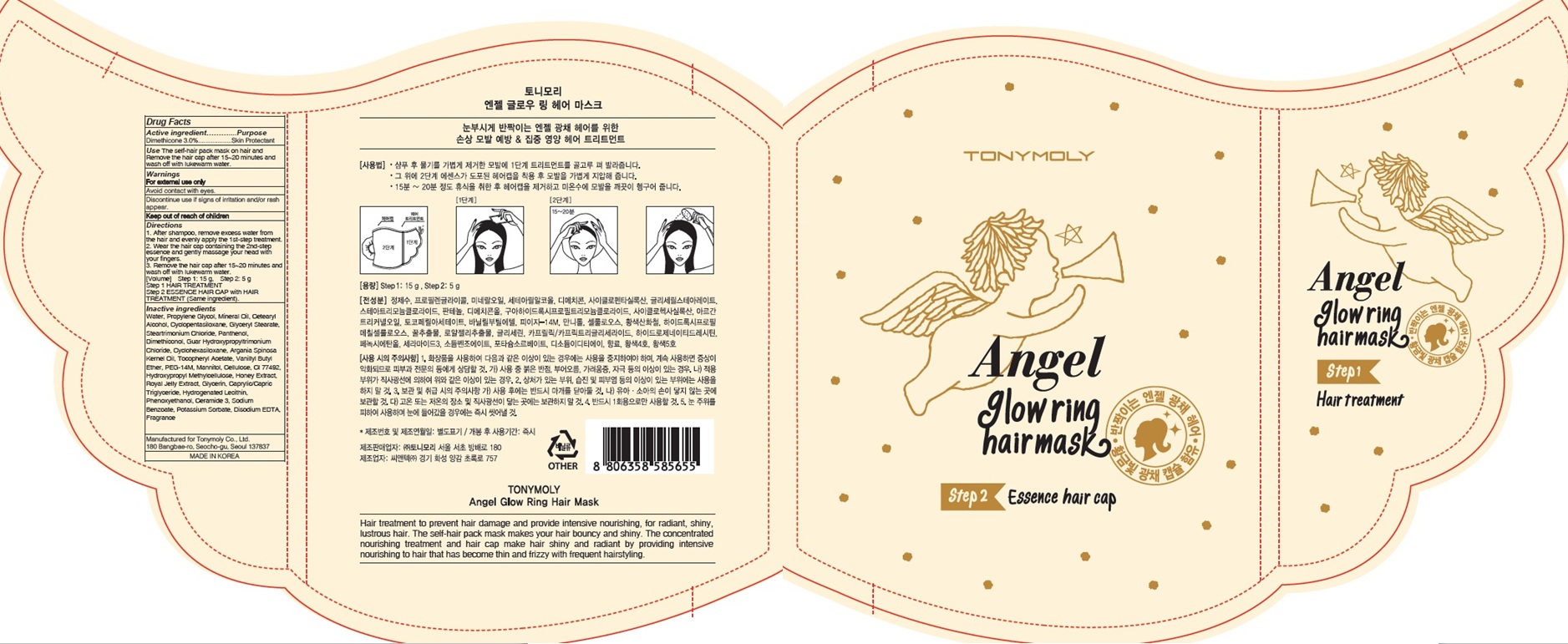 DRUG LABEL: ANG EL GLOWR ING HAIR MASK
NDC: 59078-313 | Form: PATCH
Manufacturer: TONYMOLY CO.,LTD
Category: otc | Type: HUMAN OTC DRUG LABEL
Date: 20160616

ACTIVE INGREDIENTS: Dimethicone 0.6 g/20 g
INACTIVE INGREDIENTS: Water; Propylene Glycol

ACTIVE INGREDIENT

Active ingredient: Dimethicone 3.0%

INACTIVE INGREDIENT

Inactive Ingredient: Water, Propylene Glycol, Mineral Oil, Cetearyl Alcohol, Cyclopentasiloxane, Glyceryl Stearate, Steartrimonium Chloride, Panthenol, Dimethiconol, Guar Hydroxypropyltrimonium Chloride, Cyclohexasiloxane, Argania Spinosa Kernel Oil, Tocopheryl Acetate, Vanillyl Butyl Ether, PEG-14M, Mannitol, Cellulose, CI 77492, Hydroxypropyl Methylcellulose, Honey Extract, Royal Jelly Extract, Glycerin, Caprylic/Capric Triglyceride, Hydrogenated Lecithin, Phenoxyethanol, Ceramide 3, Sodium Benzoate, Potassium Sorbate, Disodium EDTA, Fragrance

PURPOSE

Purpose: Skin Protectant

Warnings

Warnings: For external use only Avoid contact with eyes. Discontinue use if signs of irritation and/or rash appear. Keep out of reach of children

KEEP OUT OF REACH OF CHILDREN

Use

Use: The self-hair pack mask on hair and Remove the hair cap after 15~20 minutes and wash off with lukewarm water.

Directions

Directions: 1. After shampoo, remove excess water from the hair and evenly apply the 1st-step treatment. 2. Wear the hair cap containing the 2nd-step essence and gently massage your head with your fingers. 3. Remove the hair cap after 15~20 minutes and wash off with lukewarm water.